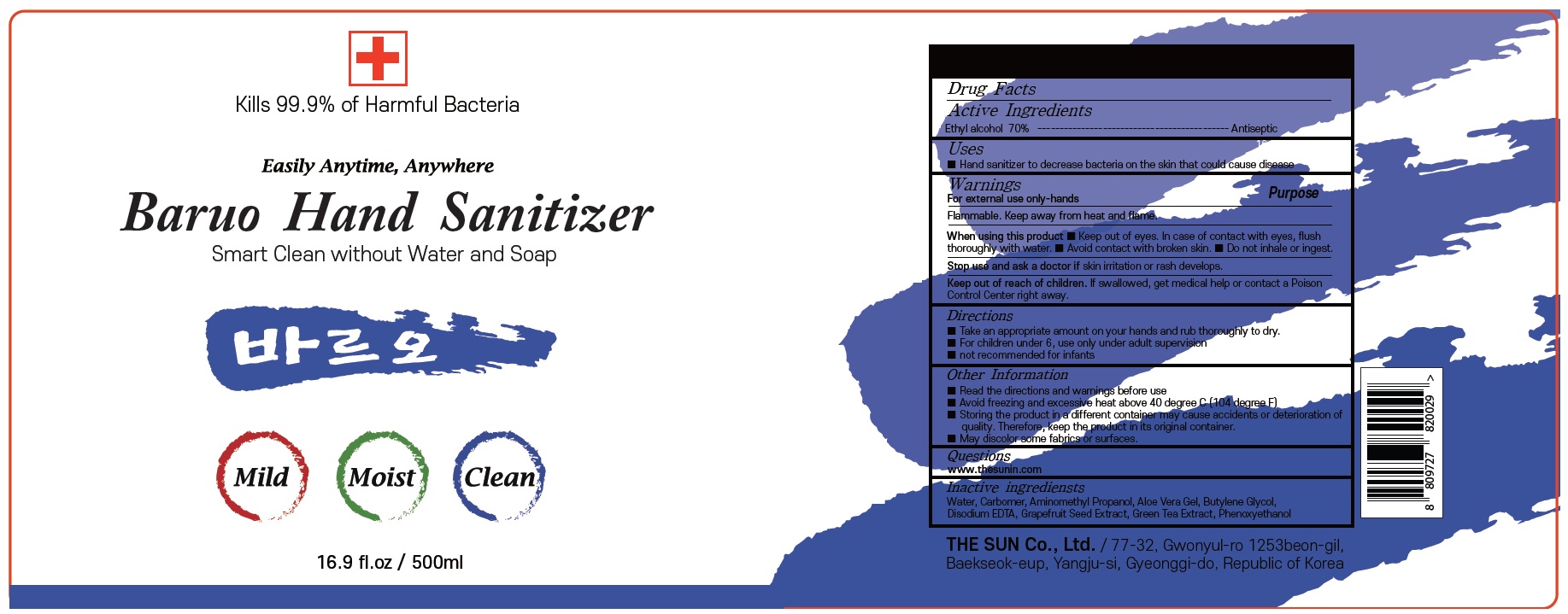 DRUG LABEL: Baruo Hand Sanitizer
NDC: 74923-030 | Form: GEL
Manufacturer: THE SUN CO.LTD
Category: otc | Type: HUMAN OTC DRUG LABEL
Date: 20200414

ACTIVE INGREDIENTS: Alcohol 320 g/500 mL
INACTIVE INGREDIENTS: Water; CARBOMER HOMOPOLYMER, UNSPECIFIED TYPE; AMINOMETHYLPROPANOL; ALOE VERA LEAF; Butylene Glycol; EDETATE DISODIUM ANHYDROUS; CITRUS PARADISI SEED; GREEN TEA LEAF; Phenoxyethanol

ACTIVE INGREDIENT

Active ingredients: Ethyl alcohol 70.0 %v/v

INACTIVE INGREDIENT

Inactive ingredients:

Water, Carbomer, Aminomethyl Propanol, Aloe Vera Gel, Butylene Glycol, Disodium EDTA, Grapefruit Seed Extract, Green Tea Extract, Phenoxyethanol

PURPOSE

PURPOSE: Antiseptic

WARNINGS

For external use only-hands

Flammable. Keep away from heat and flame.

When using this product ■ Keep out of eyes. In case of contact with eyes, flush thoroughly with water. ■ Avoid contact with broken skin. ■ Do not inhale or ingest.

Stop use and ask a doctor if skin irritation or rash develops.

Keep out of reach of children. If swallowed, get medical help or contact a
Poison Control Center right away.

Uses

■ Hand sanitizer to decrease bacteria on the skin that could cause disease

Directions

■ Take an appropriate amount on your hands and rub thoroughly to dry.
■ For children under 6, use only under adult supervision
■ not recommended for infants

Other Information

■ Read the directions and warnings before use
■ Avoid freezing and excessive heat above 40 degree C (104 degree F)
■ Storing the product in a different container may cause accidents or
deterioration of quality. Therefore, keep the product in its original container.
■ May discolor some fabrics or surfaces.

QUESTIONS

www thesunin.com